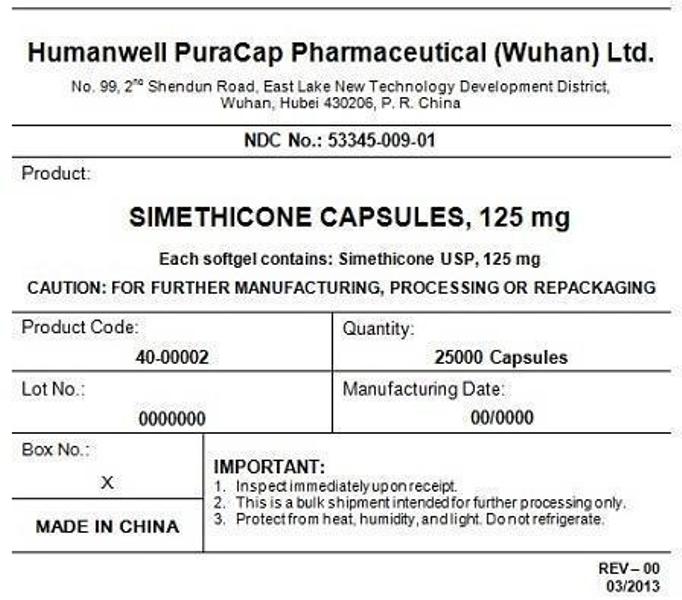 DRUG LABEL: Simethicone
NDC: 53345-009 | Form: CAPSULE, LIQUID FILLED
Manufacturer: Humanwell PuraCap Pharmaceutical (Wuhan), Ltd.
Category: otc | Type: HUMAN OTC DRUG LABEL
Date: 20241121

ACTIVE INGREDIENTS: DIMETHICONE 125 mg/1 1
INACTIVE INGREDIENTS: SILICON DIOXIDE; FD&C BLUE NO. 1; FD&C RED NO. 40; D&C YELLOW NO. 10; GELATIN; GLYCERIN; PEPPERMINT OIL; TITANIUM DIOXIDE; WATER

Active ingredient (in each capsule)

Simethicone 125 mg

Purpose

Antiflatulent

Usesfor relief of:

- bloating
- pressure
- fullness
- stuffed feeling commonly referred to as gas

Warnings

Stop use and ask a doctorifcondition persists.

PREGNANCY OR BREAST FEEDING

If pregnant or breast-feeding,ask a health care professional before use.

Keep out of reach of children.

OVERDOSAGE

In case of overdose, get medical help or contact a Poison Control Center right away.

Directions

- adults:swallow with water 1 or 2 softgels as needed after meals or at bedtime
- do not exceed 4 softgels per day unless directed by doctor

Other information

- store at controlled room temperature 15°-30°C (59°-86°F)
- protect from heat and moisture
- do not use if imprinted safety seal under cap is broken or missing

Inactive ingredients

D&C Yellow #10, FD&C Blue #1, FD&C Red #40, gelatin, glycerin, peppermint oil, purified water, titanium dioxide and white edible ink

Manufactured by:
Humanwell PuraCap Pharmaceutical (Wuhan) Ltd.
Wuhan, Hubei
430206, China

PRINCIPAL DISPLAY PANEL - Shipping Label

SIMETHICONE CAPSULES, 125 mg

Quantity : 25000 Capsules
NDC. No : 53345-009-01

IMPORTANT:

Inspect immediate upon receipt.
This is a bulk shipment intended for further processing only.
Protect from heat, humidity, and light. Do not refrigerate.

CAUTION : "FOR FURTHER MANUFACTURING, PROCESSING OR REPACKING"